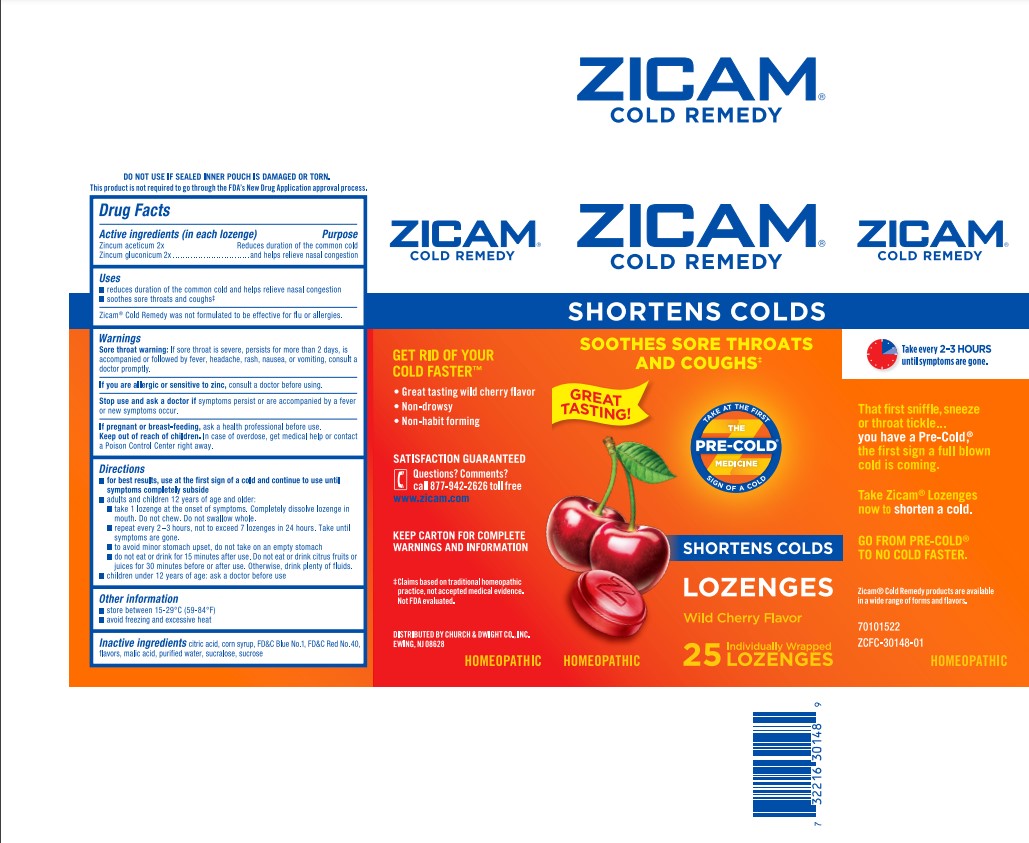 DRUG LABEL: Zicam Cold Remedy
NDC: 10237-473 | Form: LOZENGE
Manufacturer: Church & Dwight Co., Inc.
Category: homeopathic | Type: HUMAN OTC DRUG LABEL
Date: 20220328

ACTIVE INGREDIENTS: ZINC ACETATE ANHYDROUS 2 [hp_X]/1 1; ZINC GLUCONATE 2 [hp_X]/1 1
INACTIVE INGREDIENTS: CITRIC ACID MONOHYDRATE; CORN SYRUP; FD&C BLUE NO. 1; FD&C RED NO. 40; MALIC ACID; WATER; SUCRALOSE; SUCROSE

Zicam® Cold Remedy Lozenges - Wild Cherry

Drug Facts

Active ingredients (in each lozenge)

Zincum aceticum 2x

Zincum gluconicum 2x

Purpose

Reduces duration of the common cold and helps relieve nasal congestion

Uses

- reduces duration of the common cold and helps relieve nasal congestion
- soothes sore throats and coughs

Zicam® Cold Remedy was not formulated to be effective for flu or allergies.

Warnings

Sore throat warning

If sore throat is severe, persists for more than 2 days, is accompanied or followed by fever, headache, rash, nausea, or vomiting, consult a doctor promptly.

ASK DOCTOR

If you are allergic or sensitive to zinc, consult a doctor before using.

Stop use and ask a doctor if symptoms persist or are accompanied by a fever or new symptoms occur.

PREGNANCY OR BREAST FEEDING

If pregnant or breast-feeding, ask a health professional before use.

Keep out of reach of children. In case of overdose, get medical help or contact a Poison Control Center right away.

Directions

- for best results, use at the first sign of a cold and continue to use until symptoms completely subside
- adults and children 12 years of age and older:
  - take 1 lozenge at the onset of symptoms. Completely dissolve lozenge in mouth. Do not chew. Do not swallow whole.
  - repeat every 2 – 3 hours, not to exceed 7 lozenges in 24 hours. Take until symptoms are gone.
  - to avoid minor stomach upset, do not take on an empty stomach
  - do not eat or drink for 15 minutes after use. Do not eat or drink citrus fruits or juices for 30 minutes before or after use. Otherwise, drink plenty of fluids.
- children under 12 years of age: ask a doctor before use

Other information

- store between 15-29°C (59-84°F)
- avoid freezing and excessive heat

Inactive ingredients

citric acid, corn syrup, FD&C Blue No. 1, FD&C Red No. 40, flavors, malic acid, purified water, sucralose, sucrose

PRINCIPAL DISPLAY PANEL - 25 Lozenge Pouch Carton

ZICAM®

COLD REMEDY

SHORTENS COLDS
SOOTHES SORE THROATS
AND COUGHS +

GREAT TASTING!

TAKE AT THE FIRST
SIGN OF A COLD
THE
PRE-COLD®
MEDICINE

SHORTENS COLDS

LOZENGES

Wild Cherry Flavor

HOMEOPATHIC
25
Individually Wrapped
LOZENGES